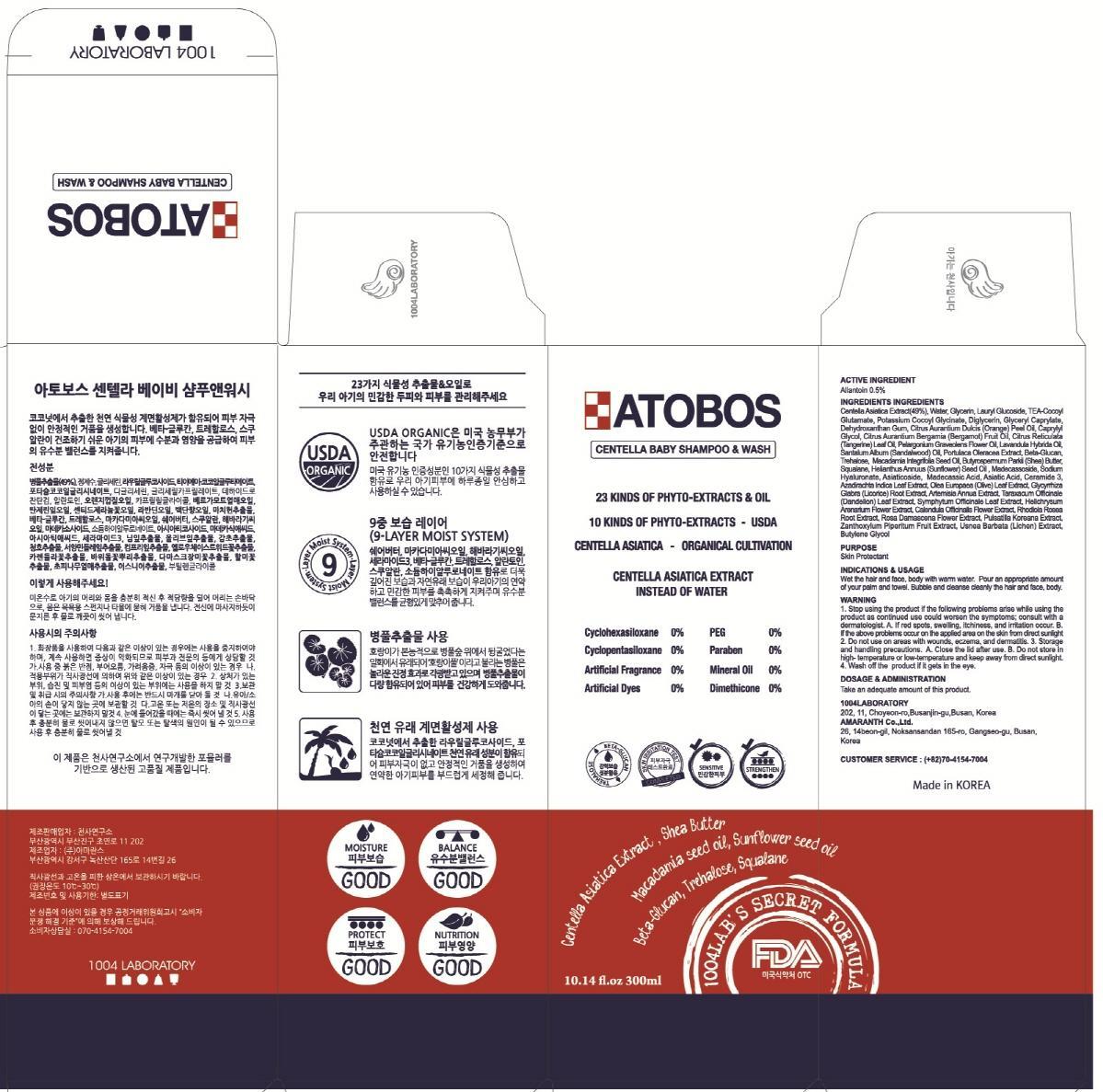 DRUG LABEL: ATOBOS CENTELLA AND WASH
NDC: 69739-110 | Form: SHAMPOO
Manufacturer: 1004LABORATORY
Category: otc | Type: HUMAN OTC DRUG LABEL
Date: 20150831

ACTIVE INGREDIENTS: Allantoin 1.5 mg/300 mL
INACTIVE INGREDIENTS: Centella Asiatica; Water

ACTIVE INGREDIENT

Active Ingredient: Allantoin 0.5%

INACTIVE INGREDIENT

Inactive Ingredients: Centella Asiatica Extract(49%), Water, Glycerin, Lauryl Glucoside, TEA-Cocoyl Glutamate, Potassium Cocoyl Glycinate, Diglycerin, Glyceryl Caprylate, Dehydroxanthan Gum, Citrus Aurantium Dulcis (Orange) Peel Oil, Caprylyl Glycol, Citrus Aurantium Bergamia (Bergamot) Fruit Oil, Citrus Reticulata (Tangerine) Leaf Oil, Pelargonium Graveolens Flower Oil, Lavandula Hybrida Oil, Santalum Album (Sandalwood) Oil, Portulaca Oleracea Extract, Beta-Glucan, Trehalose, Macadamia Integrifolia Seed Oil, Butyrospermum Parkii (Shea) Butter, Squalane, Helianthus Annuus (Sunflower) Seed Oil , Madecassoside, Sodium Hyaluronate, Asiaticoside, Madecassic Acid, Asiatic Acid, Ceramide 3, Azadirachta Indica Leaf Extract, Olea Europaea (Olive) Leaf Extract, Glycyrrhiza Glabra (Licorice) Root Extract, Artemisia Annua Extract, Taraxacum Officinale (Dandelion) Leaf Extract, Symphytum Officinale Leaf Extract, Helichrysum Arenarium Flower Extract, Calendula Officinalis Flower Extract, Rhodiola Rosea Root Extract, Rosa Damascena Flower Extract, Pulsatilla Koreana Extract, Zanthoxylum Piperitum Fruit Extract, Usnea Barbata (Lichen) Extract, Butylene Glycol

PURPOSE

Purpose: Skin Protectant

WARNINGS

Warnings: 1. Stop using the product if the following problems arise while using the product as continued use could worsen the symptoms; consult with a dermatologist. A. If red spots, swelling, itchiness, and irritation occur. B. If the above problems occur on the applied area on the skin from direct sunlight 2. Do not use on areas with wounds, eczema, and dermatitis. 3. Storage and handling precautions. A. Close the lid after use. B. Do not store in high- temperature or low-temperature and keep away from direct sunlight. 4. Wash off the product if it gets in the eye.

KEEP OUT OF REACH OF CHILDREN

INDICATIONS & USAGE

Indications & Usage: Wet the hair and face, body with warm water. Pour an appropriate amount of your palm and towel. Bubble and cleanse cleanly the hair and face, body.

DOSAGE & ADMINISTRATION

Dosage & Administration: Take an adequate amount of this product.